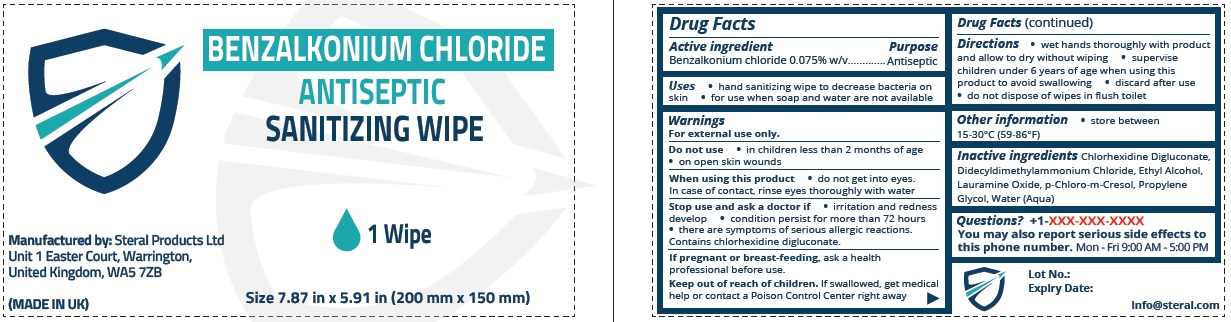 DRUG LABEL: STERAL ANTISEPTIC SANITIZING WIPE
NDC: 82045-050 | Form: CLOTH
Manufacturer: STERAL PRODUCTS LIMITED
Category: otc | Type: HUMAN OTC DRUG LABEL
Date: 20210707

ACTIVE INGREDIENTS: BENZALKONIUM CHLORIDE 0.75 mg/1 mL
INACTIVE INGREDIENTS: CHLORHEXIDINE GLUCONATE; DIDECYLDIMONIUM CHLORIDE; ALCOHOL; LAURAMINE OXIDE; CHLOROCRESOL; PROPYLENE GLYCOL; WATER

BENZALKONIUM CHLORIDE ANTISEPTIC SANITIZING WIPE

Active Ingredient

Benzalkonium chloride 0.075% w/v

Purpose

Antiseptic

Uses

• hand sanitizing wipe to decrease bacteria on skin • for use when soap and water are not available

Warnings

For external use only.
Do not use • in children less than 2 months of age • on open skin wounds

When using this product • do not get into eyes.
In case of contact, rinse eyes thoroughly with water

Stop use and ask a doctor if • irritation and redness develop • condition persist for more than 72 hours • there are symptoms of serious allergic reactions.
Contains chlorhexidine digluconate.

If pregnant or breast-feeding, ask a health professional before use.

Keep out of reach of children. If swallowed, get medical help or contact a Poison Control Center right away

Directions

• wet hands thoroughly with product and allow to dry without wiping • supervise children under 6 years of age when using this product to avoid swallowing • discard after use • do not dispose of wipes in flush toilet

Other information

• store between 15-30°C (59-86°F)

Inactive ingredients

Chlorhexidine Digluconate, Didecyldimethylammonium Chloride, Ethyl Alcohol, Lauramine Oxide, p-Chloro-m-Cresol, Propylene Glycol, Water (Aqua)

Questions?

+1-XXX-XXX-XXXX
You may also report serious side effects to this phone number. Mon - Fri 9:00 AM - 5:00 PM

1 Wipe

Size 7.87 in x 5.91 in (200 mm x 150 mm)

Manufactured by: Steral Products Ltd
Unit 1 Easter Court, Warrington,
United Kingdom, WA5 7ZB

(MADE IN UK)

Lot No.:
Expiry Date:

info@steral.com